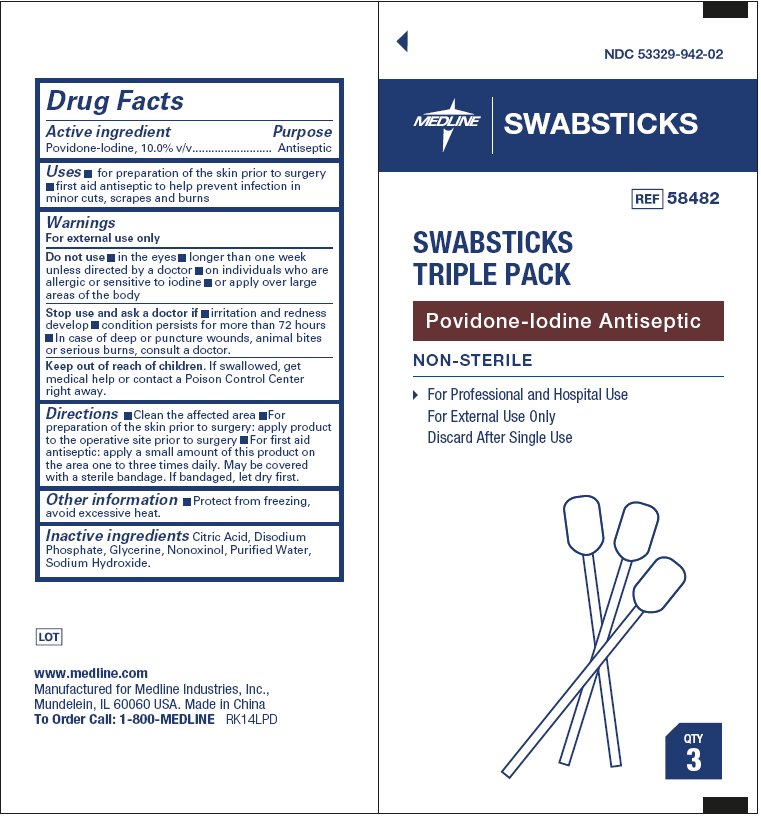 DRUG LABEL: Swabsticks Triple Pack
NDC: 53329-942 | Form: SWAB
Manufacturer: Medline Industries, Inc.
Category: otc | Type: HUMAN OTC DRUG LABEL
Date: 20150219

ACTIVE INGREDIENTS: POVIDONE-IODINE 10 mg/100 mg
INACTIVE INGREDIENTS: CITRIC ACID MONOHYDRATE; SODIUM PHOSPHATE, DIBASIC, ANHYDROUS; GLYCERIN; NONOXYNOL-10; WATER; SODIUM HYDROXIDE

Drug Facts

Active ingredient

Povidone-Iodine solution 10.0% v/v

Purpose

Antiseptic

Uses

For preparation of the skin prior to surgery

First aid antiseptic to help prevent infection in minor cuts, scrapes and burns

Warnings

For external use only

Do not use

- in the eyes
- Longer than one week unless directed by a doctor
- On individuals who are allergic or sensitive to iodine
- Or apply over large areas of the body

Stop use and ask a doctor if

- irritation and redness develop
- symptoms last for more than 72 hours
- in case of deep puncture wounds, animal bites or serious burns, consult a doctor

Keep out of reach of children.

If swallowed, get medical help or contact a Poison Control Center right away.

Directions

- Clean the affected area
- For preparation of the skin prior to surgery: apply product to the operative site prior to surgery
- For first aid antiseptic: apply a small amount of this product on the area one to three times daily. May be covered with a sterile bandage. If bandaged, let dry first

Other information

- Protect from freezing
- Avoid excessive heat

Inactive ingredients

Citric Acid, Disodium Phosphate, Glycerine, Nonoxinol, Purified Water, Sodium Hydroxide

Questions?

www.medline.com

Manufactured for Medline Industires, Inc.,

Mundelein, IL 60060 USA. Made in China

To Order Call: 1-800-MEDLINE RK14LPD

Package Label - Box Principal Display Panel top

NDC 53329-942-02

Medline

Swabsticks

REF 58482

Swabsticks Triple Pack

Povidone Iodine Antiseptic

Non-Sterile

- For Professional and Hospital Use
- For External Use Only
- Discard after single use

QTY 3